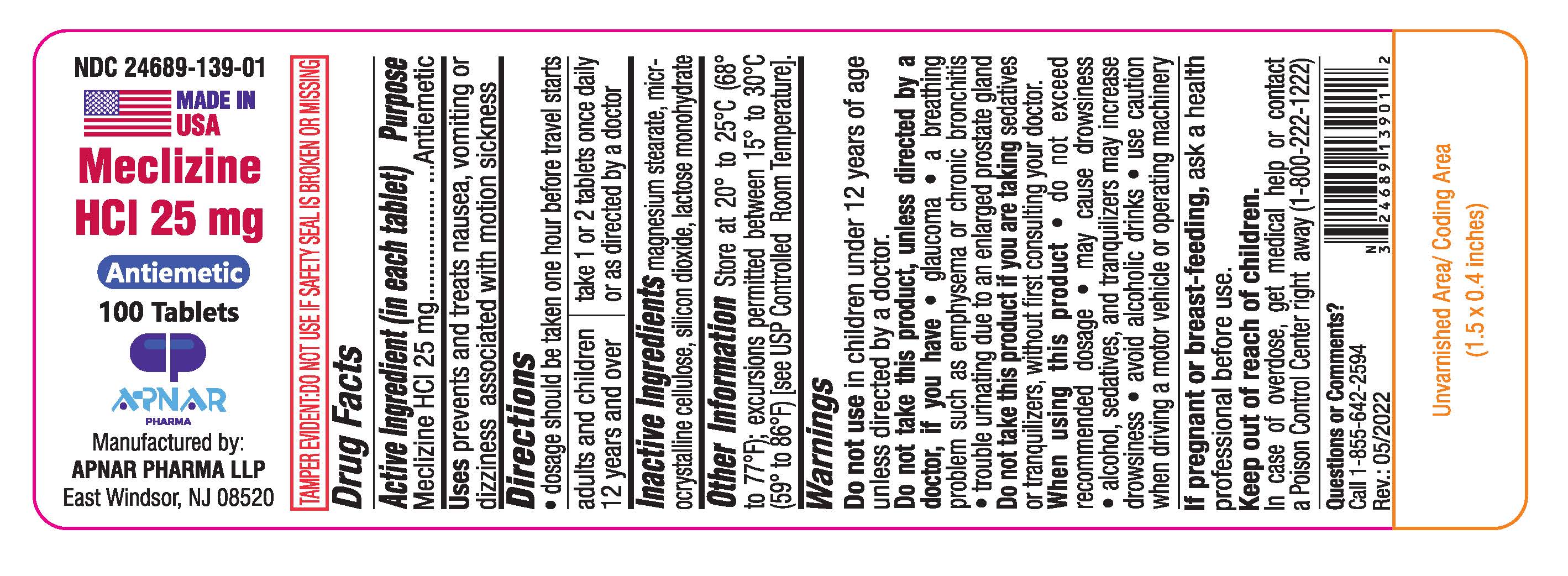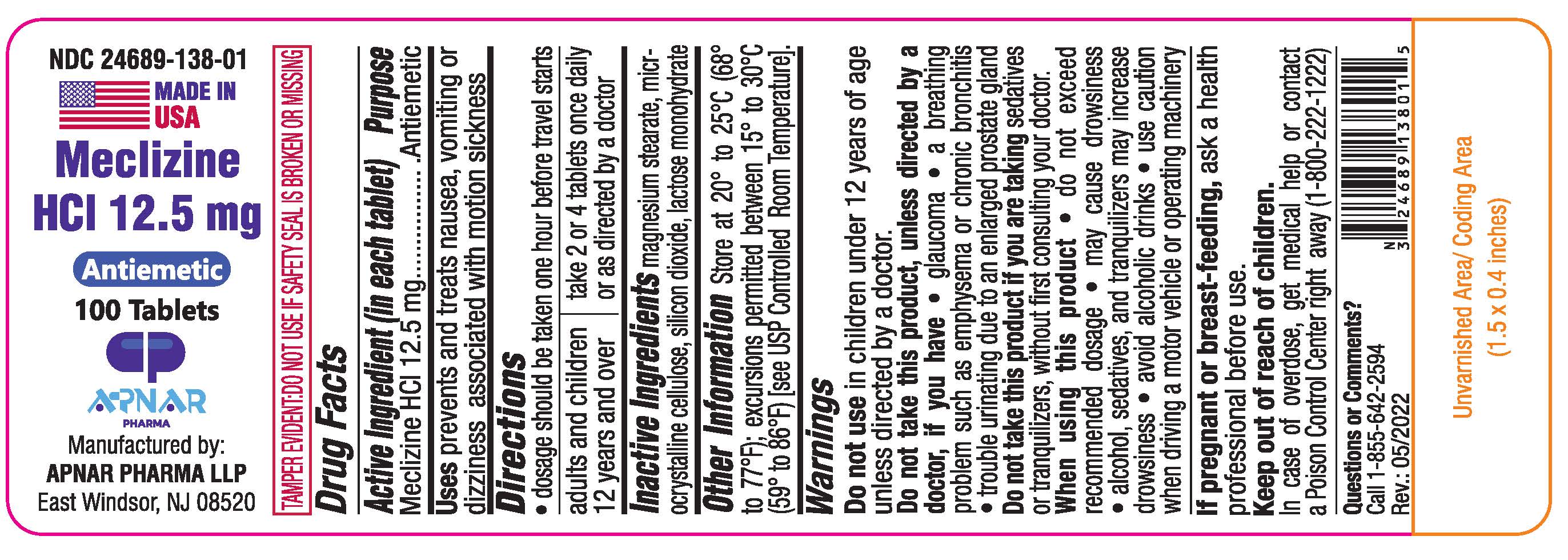 DRUG LABEL: Meclizine Hydrochloride
NDC: 24689-138 | Form: TABLET
Manufacturer: APNAR PHARMA LP
Category: otc | Type: HUMAN OTC DRUG LABEL
Date: 20250109

ACTIVE INGREDIENTS: MECLIZINE HYDROCHLORIDE 12.5 mg/1 1
INACTIVE INGREDIENTS: MAGNESIUM STEARATE; SILICON DIOXIDE; LACTOSE MONOHYDRATE; MICROCRYSTALLINE CELLULOSE

Meclizine Hydrochloride Tablets

Active Ingredient (in each tablet)

12.5mg tablet: Meclizine HCL.... 12.5 mg

25mg tablet : Meclizine HCL .....25 mg

Purpose

Antiemetic

Uses

Prevents and treats nausea, vomiting or dizziness associated with motion sickness

Directions

Meclizine HCL 12.5mg tablet :

Dosage should be taken one hour before travel starts -adults & children 12 years and over: take 2 or 4 tablets once daily or as directed by a doctor

Meclizine HCL 25mg tablet:

Dosage should be taken one hour before travel starts -adults & children 12 years and over: take 1 or 2 tablets once daily or as directed by a doctor

Inactive Ingredients

Magnesium stearate, microcrystalline cellulose,silicon dioxide, lactose monohydrate

Other Information:

store at 20°to 25°C (68°to 77°F), excursions permitted between 15°to 30°C (59°to 86°F) [see USP controlled room temperature]

Do not use in children under 12 years of age unless directed by a doctor

Do not take this product, unless directed by a doctor, if you have

- Glaucoma
- A breathing problem such as emphysema or chronic bronchitis
- Trouble urination due to an enlarged prostate gland

Do not take this product if you are taking

Sedatives or tranquilizers, without first consulting your doctor.

When using this product,

- Do not exceed recommended dosage
- may cause drowsiness
- alcohol, sedatives and tranquilizers may increase drowsiness
- avoid alcoholic drinks
- use caution when driving a motor vehicle or operating machinery

If pregnant or breast-feeding,

ask a health professional before use

Keep out of reach of children.

In case of overdose, get medical help or contact a Poison Control Center right away (1-800-222-1222)

Questions or Comments?

Call 1-855-642-2594

Rev.: 05/2022

Made in USA

Manufactured by:

APNAR PHARMA LLP

East Windsor, NJ 08520

BOXED WARNING

TAMPER EVIDENT: DO NOT USE IF SAFETY SEAL IS BROKEN OR MISSING

PACKAGE LABEL

NDC : 24689-138-01

Meclizine Hydrochloride Tablets 12.5 mg

Antiemetic

100 Tablets

NDC : 24689-139-01

Meclizine Hydrochloride Tablets 25 mg

Antiemetic

100 Tablets